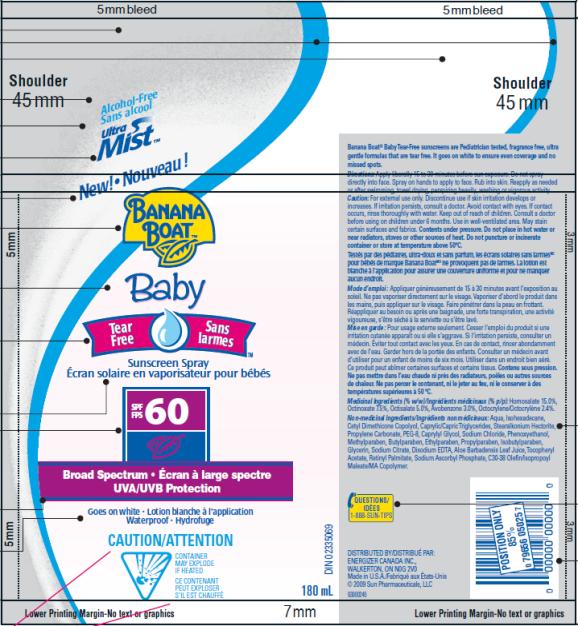 DRUG LABEL: Banana Boat Baby Tear Free Sunscreen SPF 60
NDC: 17630-2001 | Form: SPRAY
Manufacturer: Accra-Pac, Inc.
Category: otc | Type: HUMAN OTC DRUG LABEL
Date: 20100319

ACTIVE INGREDIENTS: HOMOSALATE 0.15 mL/1 mL; OCTINOXATE 0.075 mL/1 mL; OCTISALATE 0.05 mL/1 mL; AVOBENZONE 0.03 mL/1 mL; OCTOCRYLENE 0.024 mL/1 mL
INACTIVE INGREDIENTS: MEDIUM-CHAIN TRIGLYCERIDES; PROPYLENE CARBONATE; CAPRYLYL GLYCOL; SODIUM CHLORIDE; PHENOXYETHANOL; METHYLPARABEN; BUTYLPARABEN; ETHYLPARABEN; PROPYLPARABEN; ISOBUTYLPARABEN; GLYCERIN; SODIUM CITRATE; EDETATE DISODIUM; ALOE VERA LEAF; .ALPHA.-TOCOPHEROL ACETATE, D-; VITAMIN A PALMITATE; SODIUM ASCORBYL PHOSPHATE; POLYETHYLENE GLYCOL 400

Banana Boat Baby Tear Free Sunscreen Spray SPF 60

Active Ingredients

Homosalate 0.15mL / 1mL

Octinoxate 0.075mL / 1mL

Octisalate 0.05mL / 1mL

Avobenzone 0.03mL / 1mL

Octocrylene 0.024mL / 1mL

Purpose

Sunscreen

Directions:

Apply liberally 15 to 30 minutes before sun exposure. Do not spray directly into face. Spray on hands to apply to face. Rub into skin. Reapply as needed or after swimming, towel drying, perspiring heavily, washing or vigorous activity.

Caution:

For external use only. Discontinue use if skin irritation develops or increases. If irritation persists, consult a doctor. Avoid contact with eyes. If contact occurs, rinse thoroughly with water. Keep out of reach of children. Consult a doctor before using on children under 6 months. Use in well-ventilated area. May stain certain surfaces and fabrics. Contents under pressure. Do not place in hot water or near radiators, stoves or other sources of heat. Do not puncture or incinerate container or store at temperature above 50ºC.

Mode d’emploi :

Appliquer généreusement de 15 à 30 minutes avant l’exposition au soleil. Ne pas vaporiser directement sur le visage. Vaporiser d’abord le produit dans les mains, puis appliquer sur le visage. Faire pénétrer dans la peau en frottant. Réappliquer au besoin ou après une baignade, une forte transpiration, une activité vigoureuse, s’être séché à la serviette ou s’être lavé.

Mise en garde :

Pour usage externe seulement. Cesser l’emploi du produit si une irritation cutanée apparaît ou si elle s’aggrave. Si l’irritation persiste, consulter un médecin. Éviter tout contact avec les yeux. En cas de contact, rincer abondamment avec de l’eau. Garder hors de la portée des enfants. Consulter un médecin avant d’utiliser pour un enfant de moins de six mois. Utiliser dans un endroit bien aéré. Ce produit peut abîmer certaines surfaces et certains tissus. Contenu sous pression. Ne pas mettre dans l’eau chaude ni près des radiateurs, poêles ou autres sources de chaleur. Ne pas percer le contenant, ni le jeter au feu, ni le conserver à des températures supérieures à 50 ºC.

Medicinal Ingredients (% w/w)/Ingrédients médicinaux (% p/p):

Homosalate 15.0%, Octinoxate 7.5%, Octisalate 5.0%, Avobenzone 3.0%, Octocrylene/Octocrylène 2.4%.

Non-medicinal Ingredients/Ingrédients non médicinaux:

Aqua, Isohexadecane, Cetyl Dimethicone Copolyol, Caprylic/Capric Triglycerides, Stearalkonium Hectorite, Propylene Carbonate, PEG-8, Caprylyl Glycol, Sodium Chloride, Phenoxyethanol, Methylparaben, Butylparaben, Ethylparaben, Propylparaben, Isobutylparaben, Glycerin, Sodium Citrate, Disodium EDTA, Aloe Barbadensis Leaf Juice, Tocopheryl Acetate, Retinyl Palmitate, Sodium Ascorbyl Phosphate, C30-38 Olefin/Isopropoyl Maleate/MA Copolymer.

QUESTIONS/IDÉES

1-888-SUN-TIPS

DISTRIBUTED BY/DISTRIBUÉ PAR:
ENERGIZER CANADA INC.,
WALKERTON, ON N0G 2V0
Made in U.S.A./Fabriqué aux États-Unis
2009 Sun Pharmaceuticals, LLC

PRINCIPAL DISPLAY PANEL

Alcohol-Free
Sans Alcool
UltraMist TM
New! Nouveau!
Banana Boat TM
Baby
Tear Free
Sans Iarmes
Sunscreen Spray
Écran solaire en vaporisateur pour bébés
SPF/FPS 60
Broad Spectrum Écran à large spectre
UVA/UVB Protection
Goes on white Lotion blanche à l’application
Waterproof Hydrofuge